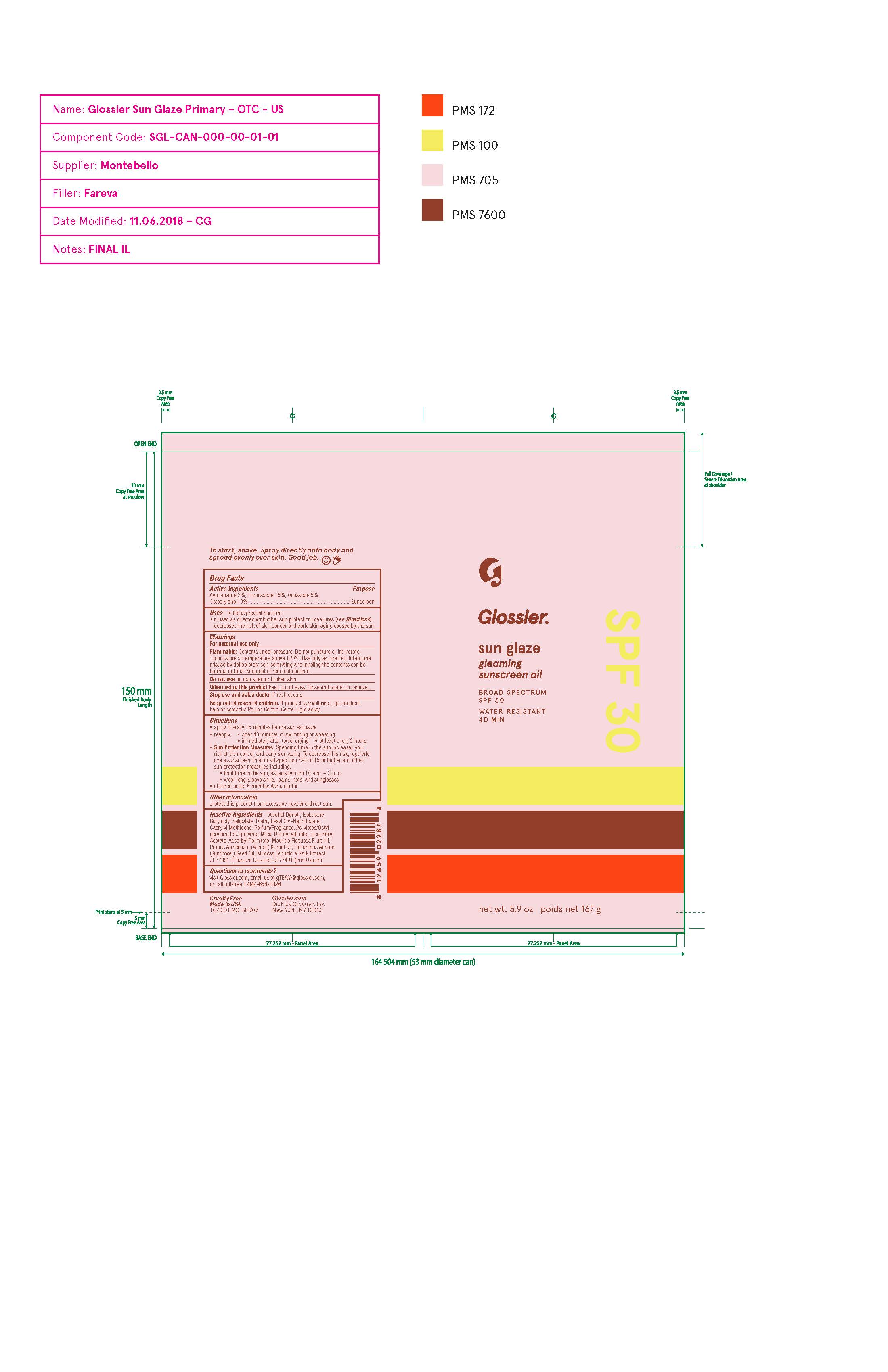 DRUG LABEL: Glossier sun glaze gleaming sunscreen oil broad spectrum SPF 30 Water Resistant 40 Min
NDC: 71425-030 | Form: AEROSOL, SPRAY
Manufacturer: Glossier Inc.
Category: otc | Type: HUMAN OTC DRUG LABEL
Date: 20181113

ACTIVE INGREDIENTS: AVOBENZONE 3 g/100 g; HOMOSALATE 15 g/100 g; OCTISALATE 5 g/100 g; OCTOCRYLENE 10 g/100 g
INACTIVE INGREDIENTS: ALCOHOL; ISOBUTANE; BUTYLOCTYL SALICYLATE; DIETHYLHEXYL 2,6-NAPHTHALATE; MICA; DIBUTYL ADIPATE; .ALPHA.-TOCOPHEROL ACETATE; ASCORBYL PALMITATE; MAURITIA FLEXUOSA FRUIT OIL; PRUNUS ARMENIACA SEED; HELIANTHUS ANNUUS SEED WAX; MIMOSA TENUIFLORA BARK; TITANIUM DIOXIDE; BROWN IRON OXIDE

DRUG FACTS

Active Ingredients

Avobenzone 2.1%
Homosalate 10.50%
Octisalate 3.50%
Octocrylene 7.00%

Uses

• helps prevent sunburn • if used as directed with other
sun protection measures (see Directions), decreases the
risk of skin cancer and early skin aging caused by the sun

Warnings

For external use only
Flammable: Contents under pressure. Do not puncture or incinerate.
Do not store at temperature above 120°F. Use only as directed. Intentional
misuse by deliberately con-centrating and inhaling the contents can be
harmful or fatal. Keep out of reach of children.
Do not use on damaged or broken skin.
When using this product keep out of eyes. Rinse with water to remove.
Stop use and ask a docor if rash occurs
Keep out of reach of children. If swalled, get medical help or contact a Poison Control Center right away.

Directions

• apply generously 15 minutes before sun exposure
• reapply: •after 40 minutes of swimming or sweating
• immediately after towel drying • at least every 2 hours

• Sun Protection Measures. Spending time in the sun
increases your risk of skin cancer and early skin aging. To decrease
this risk, regularly use a sunscreen with a Broad Spectrum SPF
value of 15 or higher and other sun protection measures including:
• limit time in the sun, especially from 10 a.m. - 2 p.m.
• wear long-sleeved shirts, pants, hats, and sunglasses
• children under 6 months of age: Ask a doctor

Inactive ingredients

Alcohol Denat., Isobutane, Butyloctyl Salicylate, Diethylhexyl 2,6-Naphthalate, Caprylyl Methicone, Parfum/Fragrance, Acrylates/Octylacrylamide Copolymer, Mica, Dibutyl Adipate, Tocopheryl Acetate, Ascorbyl Palmitate, Mauritia Flexuosa Fruit Oil, Prunus Armeniaca (Apricot) Kernel Oil, Helianthus Annuus (Sunflower) Seed Oil, Mimosa Tenuiflora Bark Extract, CI 77891 (Titanium Dioxide), CI 77491 (Iron Oxides).

Other Information

• protect the product in this container from excessive
heat and direct sun

Questions or Comments?

visit Glossier.com, email us at gTEAM@glossier.com,
or call toll-free 1-844-654-8326